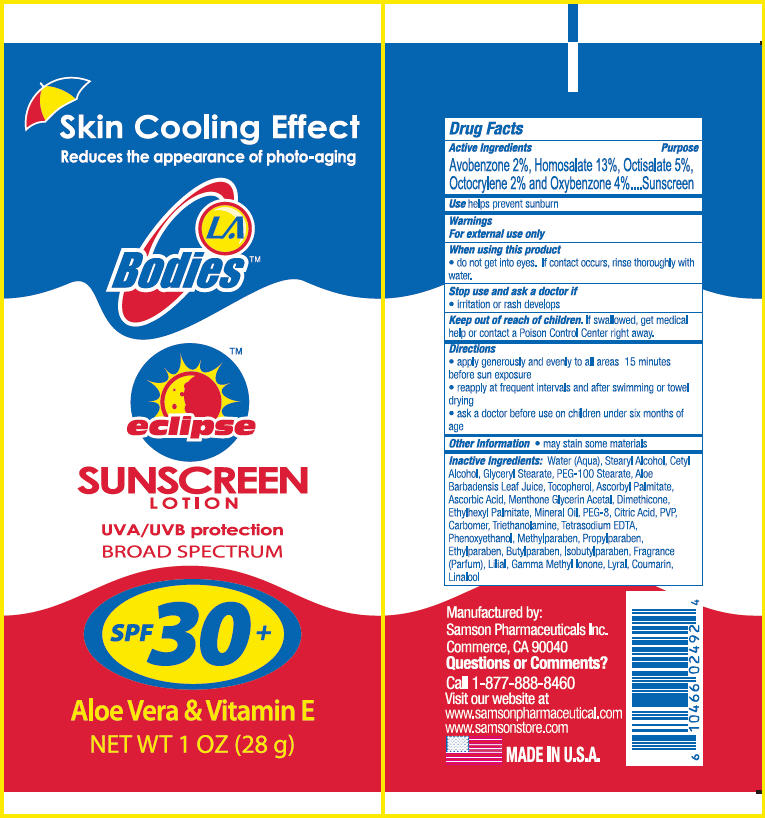 DRUG LABEL: LA Bodies Eclipse Sunscreen SPF 30
NDC: 20146-4007 | Form: LOTION
Manufacturer: SAMSON PHARMACEUTICAL
Category: otc | Type: HUMAN OTC DRUG LABEL
Date: 20240117

ACTIVE INGREDIENTS: Avobenzone 20 mg/1 g; Homosalate 130 mg/1 g; Octisalate 50 mg/1 g; Octocrylene 20 mg/1 g; Oxybenzone 40 mg/1 g
INACTIVE INGREDIENTS: water; stearyl alcohol; cetyl alcohol; glyceryl monostearate; PEG-100 stearate

LA Bodies™ Eclipse Sunscreen Lotion SPF 30

Drug Facts

Active Ingredients

Avobenzone 2%, Homosalate 13%, Octisalate 5%, Octocrylene 2% and Oxybenzone 4%

Purpose

Sunscreen

Use

helps prevent sunburn

Warnings

For external use only

When using this product

- do not get into eyes. If contact occurs, rinse thoroughly with water.

Stop use and ask a doctor if

- irritation or rash develops

Keep out of reach of children. If swallowed, get medical help or contact a Poison Control Center right away.

Directions

- apply generously and evenly to all areas 15 minutes before sun exposure
- reapply at frequent intervals and after swimming or towel drying
- ask a doctor before use on children under six months of age

Other information

- may stain some materials

Inactive Ingredients

Water (Aqua), Stearyl Alcohol, Cetyl Alcohol, Glyceryl Stearate, PEG-100 Stearate, Aloe Barbadensis Leaf Juice, Tocopherol, Ascorbyl Palmitate, Ascorbic Acid,
Menthone Glycerin Acetal, Dimethicone, Ethylhexyl Palmitate, Mineral Oil, PEG-8, Citric Acid, PVP, Carbomer, Triethanolamine, Tetrasodium EDTA, Phenoxyethanol,
Methylparaben, Propylparaben, Ethylparaben, Butylparaben, Isobutylparaben, Fragrance (Parfum), Lilial, Gamma Methyl Ionone, Lyral, Coumarin, Linalool

Questions or Comments?

Call 1-877-888-8460

Manufactured by:
Samson Pharmaceutical Inc.
Commerce, CA 90040

PRINCIPAL DISPLAY PANEL - 28 g Tube Label

Skin Cooling Effect
Reduces the appearance of photo-aging

LA
Bodies™

eclipse

SUNSCREEN
LOTION

UVA/UVB protection
BROAD SPECTRUM

SPF 30+

Aloe Vera & Vitamin E
NET WT 1 OZ (28 g)